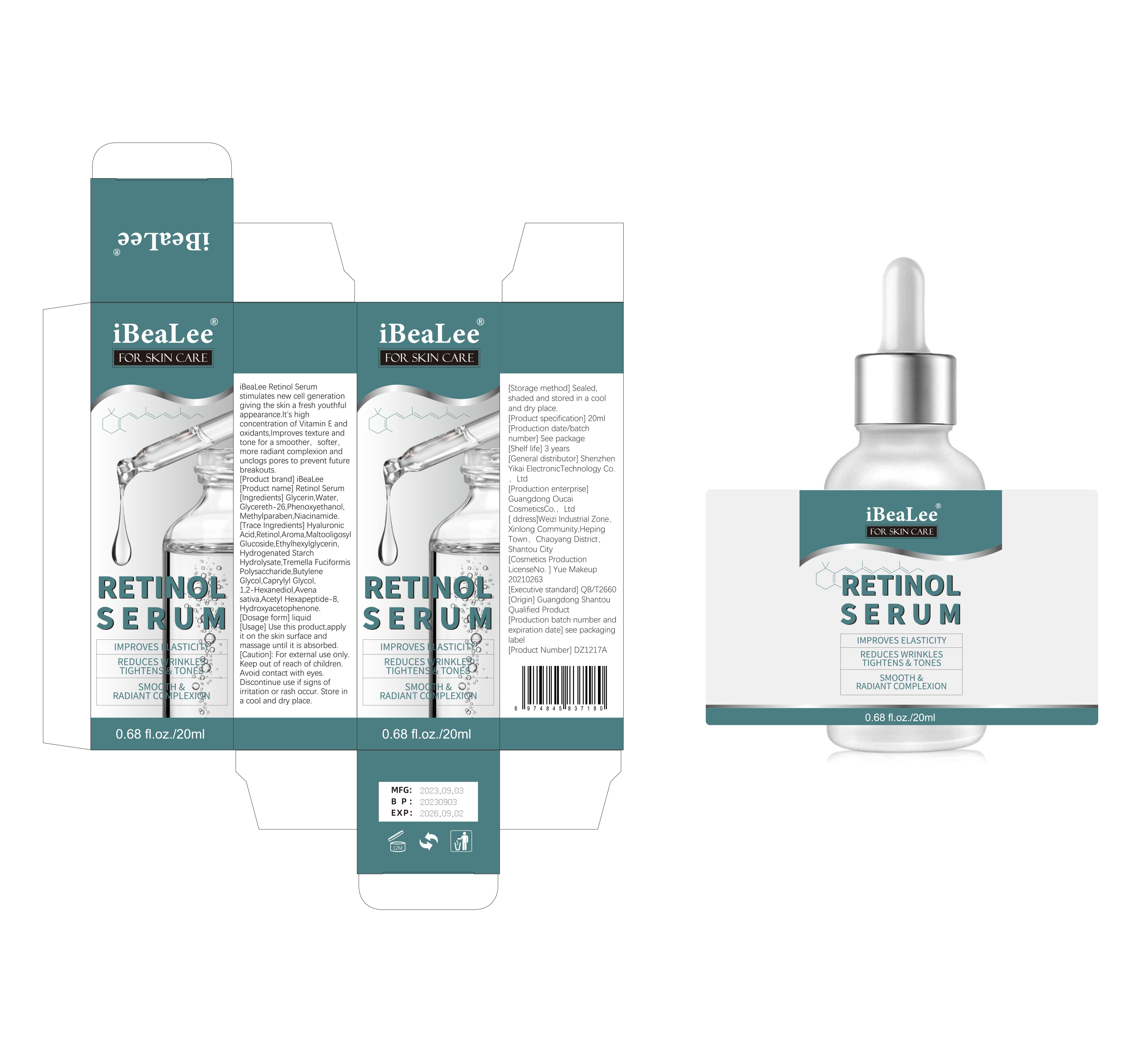 DRUG LABEL: Retinol Serum
NDC: 83809-001 | Form: LIQUID
Manufacturer: Shenzhen Yikai Electronic Technology Co., Ltd.
Category: otc | Type: HUMAN OTC DRUG LABEL
Date: 20231116

ACTIVE INGREDIENTS: RETINOL 0.1 g/100 mL
INACTIVE INGREDIENTS: GLYCERETH-26; PHENOXYETHANOL; NIACINAMIDE; BUTYLENE GLYCOL; AVENA SATIVA FLOWERING TOP; ACETYL HEXAPEPTIDE-8; GLYCERIN; METHYLPARABEN; HYALURONIC ACID; TREMELLA FUCIFORMIS FRUITING BODY; HYDROXYACETOPHENONE; ETHYLHEXYLGLYCERIN; CAPRYLYL GLYCOL; WATER; AROMADENDRIN; 1,2-HEXANEDIOL; MALTOOLIGOSYL GLUCOSIDE; HYDROGENATED STARCH HYDROLYSATE

Active Ingredient

Retinol 0.1%

Purpose

Anti-Aging

Use

iBeaLee Retinol Serum
stimulates new cell generation
giving the skin a fresh youthful
appearance.It's high
concentration of Vitamin E and
oxidants,Improves texture and
tone for a smoother, softer,
more radiant complexion and
unclogs pores to prevent future
breakouts.

Warnings

For external use only.
Keep out of reach of children.
Avoid contact with eyes.
Discontinue use if signs of
irritation or rash occur. Store in
a cool and dry place.

Stop Use

This product has not been found allergic. If allergic occurs, stop using it immediately.

Keep Oot Of Reach Of Children

Please store this product out of the reach of childre

Directions

Use this product,apply it on the skin surface and massage until it is absorbed.

Inactive ingredients

Glycerin, Water, Glycereth-26, Phenoxyethanol, Methylparaben, Niacinamide, Hyaluronic Acid, Aroma, Maltooligosyl Glucoside, Ethylhexylglycerin, Hydrogenated Starch Hydrolysate, Tremella Fuciformis Polysaccharide, Butylene Glycol, Caprylyl Glycol, 1,2-Hexanediol, Avena sativa, Acetyl Hexapeptide-8, Hydroxyacetophenone.